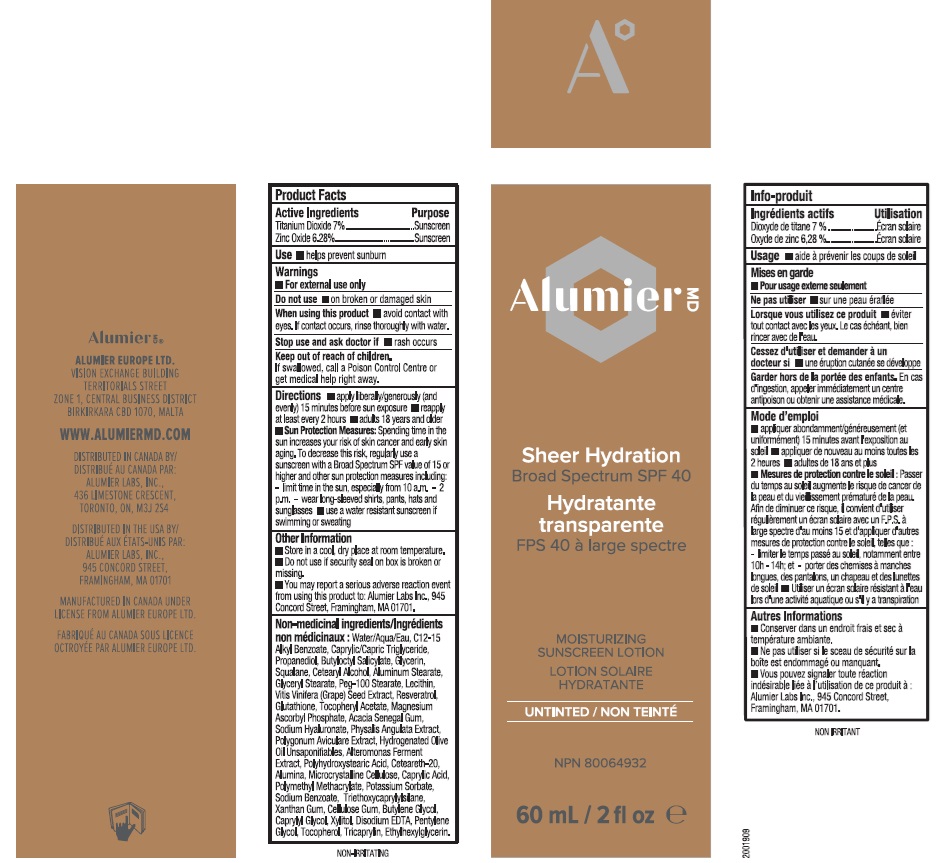 DRUG LABEL: Alumier MD Sheer Hydration
NDC: 69473-021 | Form: LOTION
Manufacturer: Alumier Labs
Category: otc | Type: HUMAN OTC DRUG LABEL
Date: 20241203

ACTIVE INGREDIENTS: ZINC OXIDE 62.8 mg/1 mL; TITANIUM DIOXIDE 70 mg/1 mL
INACTIVE INGREDIENTS: SODIUM BENZOATE; XYLITOL; PHYSALIS ANGULATA; POLYGONUM AVICULARE WHOLE; POLY(METHYL METHACRYLATE; 450000 MW); CAPRYLYL GLYCOL; POTASSIUM SORBATE; HYALURONATE SODIUM; TRICAPRYLIN; TOCOPHEROL; MEDIUM-CHAIN TRIGLYCERIDES; ALUMINUM MONOSTEARATE; TRIETHOXYCAPRYLYLSILANE; WATER; CETOSTEARYL ALCOHOL; GLYCERYL MONOSTEARATE; PEG-100 STEARATE; ACACIA; POLYOXYL 20 CETOSTEARYL ETHER; ALUMINUM OXIDE; XANTHAN GUM; SQUALANE; ALKYL (C12-15) BENZOATE; PROPANEDIOL; GLUTATHIONE; MAGNESIUM ASCORBYL PHOSPHATE; MICROCRYSTALLINE CELLULOSE; EDETATE DISODIUM; CARBOXYMETHYLCELLULOSE SODIUM, UNSPECIFIED FORM; CAPRYLIC ACID; ETHYLHEXYLGLYCERIN; PENTYLENE GLYCOL; BUTYLOCTYL SALICYLATE; GLYCERIN; VITIS VINIFERA SEED; RESVERATROL; .ALPHA.-TOCOPHEROL ACETATE; LECITHIN, SOYBEAN; HYDROGENATED OLIVE OIL UNSAPONIFIABLES; POLYHYDROXYSTEARIC ACID (2300 MW); BUTYLENE GLYCOL

Alumier MD Sheer Hydration

Active Ingredients

Titanium Dioxide 7%

Zinc Oxide 6.28%

Purpose

Sunscreen

Use

- helps prevent sunburn

Warnings

- For external use only.

Do not use

- on broken or damaged skin

When using this product

- avoid contact with eyes. If contact occurs, rinse thoroughly with water.

Stop use and ask doctor if

- rash occurs

Keep out of reach of children.

If swallowed, call a Poison Control Centre or get medical help right away.

Directions

- apply liberally/generously (and evenly) 15 minutes before sun exposure
- reapply at least every 2 hours
- adults 18 years and older
- Sun Protection Measures: Spending time in the sun increases your risk of skin cancer and early skin aging. To decrease this risk, regularly use a sunscreen with a Broad Spectrum SPF value of 15 or higher and other sun protection measures including: - limit time in the sun, especially from 10 a.m.-2 p.m. - wear long-sleeved shirts, pants, hats and sunglasses
- use a water resistant sunscreen if swimming or sweating

Other Information

- Store in a cool, dry place at room temperature.
- Do not use if security seal on box is broken or missing.
- You may report a serious adverse reaction event from using this product to: Alumier Labs Inc., 945 Concord Street, Framingham, MA 01701

Non-medicinal ingredients

Water/Aqua/Eau, C12-15 Alkyl Benzoate, Caprylic/Capric Triglyceride, Propanediol, Butyloctyl Salicylate, Glycerin, Squalane, Cetearyl Alcohol, Aluminum Stearate, Glyceryl Stearate, Peg-100 Stearate, Lecithin, Vitis Vinifera (Grape) Seed Extract, Resveratrol, Glutathione, Tocopheryl Acetate, Magnesium Ascorbyl Phosphate, Acacia Senegal Gum, Sodium Hyaluronate, Physalis Angulata Extract, Polygonum Aviculare Extract, Hydrogenated Olive Oil Unsaponifiables, Alteromonas Ferment Extract, Polyhydroxysteric Acid, Ceteareth-20, Alumina, Microcrystalline Cellulose, Caprylic Acid, Polymethyl Methacrylate, Potassium Sorbate, Sodium Benzoate, Triethoxycaprylylsilane, Xanthan Gum, Cellulose Gum, Butylene Glycol, Caprylyl Glycol, Xylitol, Disodium EDTA, Pentylene Glycol, Tocopherol, Tricaprylin, Ethylhexylglycerin.